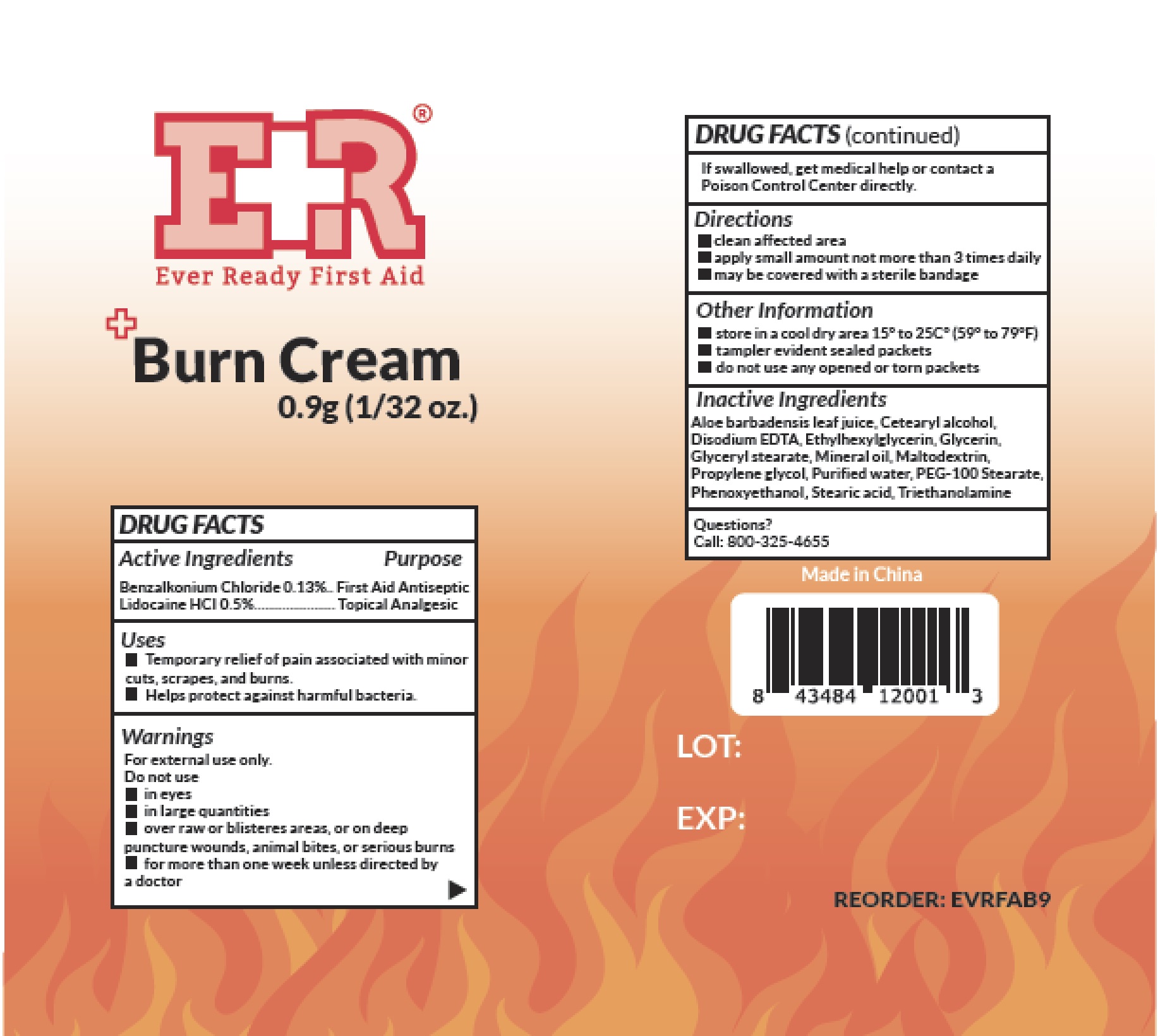 DRUG LABEL: Ever Ready First Aid
NDC: 72976-005 | Form: CREAM
Manufacturer: Ever Ready First Aid
Category: otc | Type: HUMAN OTC DRUG LABEL
Date: 20240115

ACTIVE INGREDIENTS: LIDOCAINE HYDROCHLORIDE 5 mg/1 g; BENZALKONIUM CHLORIDE 1.3 mg/1 g
INACTIVE INGREDIENTS: PHENOXYETHANOL; WATER; GLYCERIN; EDETATE DISODIUM ANHYDROUS; PROPYLENE GLYCOL; TROLAMINE; ALOE VERA LEAF; CETOSTEARYL ALCOHOL; GLYCERYL MONOSTEARATE; MINERAL OIL; MALTODEXTRIN; PEG-100 STEARATE; STEARIC ACID; ETHYLHEXYLGLYCERIN

72976-005 Ever Ready First Aid
Burn Cream

Active Ingredients

Benzalkonium Chloride 0.13%

Lidocaine HCl 0.5%

Purpose

First Aid Antiseptic

Topical Analgesic

Uses

- Temporary relief of pain associated with minor cuts, scrapes, and burns.
- Helps protect against harmful bacteria.

Warnings

For external use only.

Do not use

- in eyes
- in large quantities
- over raw or blisteres areas, or on deep puncture wounds, animal bites, or serious burns
- for more than one week unless directed by a doctor

Stop use and ask a doctor if condition worsens or persists for more than 7 days or clears up and returns.

Keep out of reach of children. If swallowed, get medical help or contact a Poison Control Center directly.

Directions

- clean affected area
- apply small amount not more than 3 times daily
- may be covered with a sterile bandage

Other Information

- store in a cool dry area 15° to 25C° (59° to 79°F)
- tampler evident sealed packets
- do not use any opened or torn packets

Inactive Ingredients

Aloe barbadensis leaf juice, Cetearyl alcohol, Disodium EDTA, Ethylhexylglycerin, Glycerin, Glyceryl stearate, Mineral oil, Maltodextrin,

Propylene glycol, Purified water, PEG-100 Stearate, Phenoxyethanol, Stearic acid, Triethanolamine

Questions?

Call: 800-325-4655